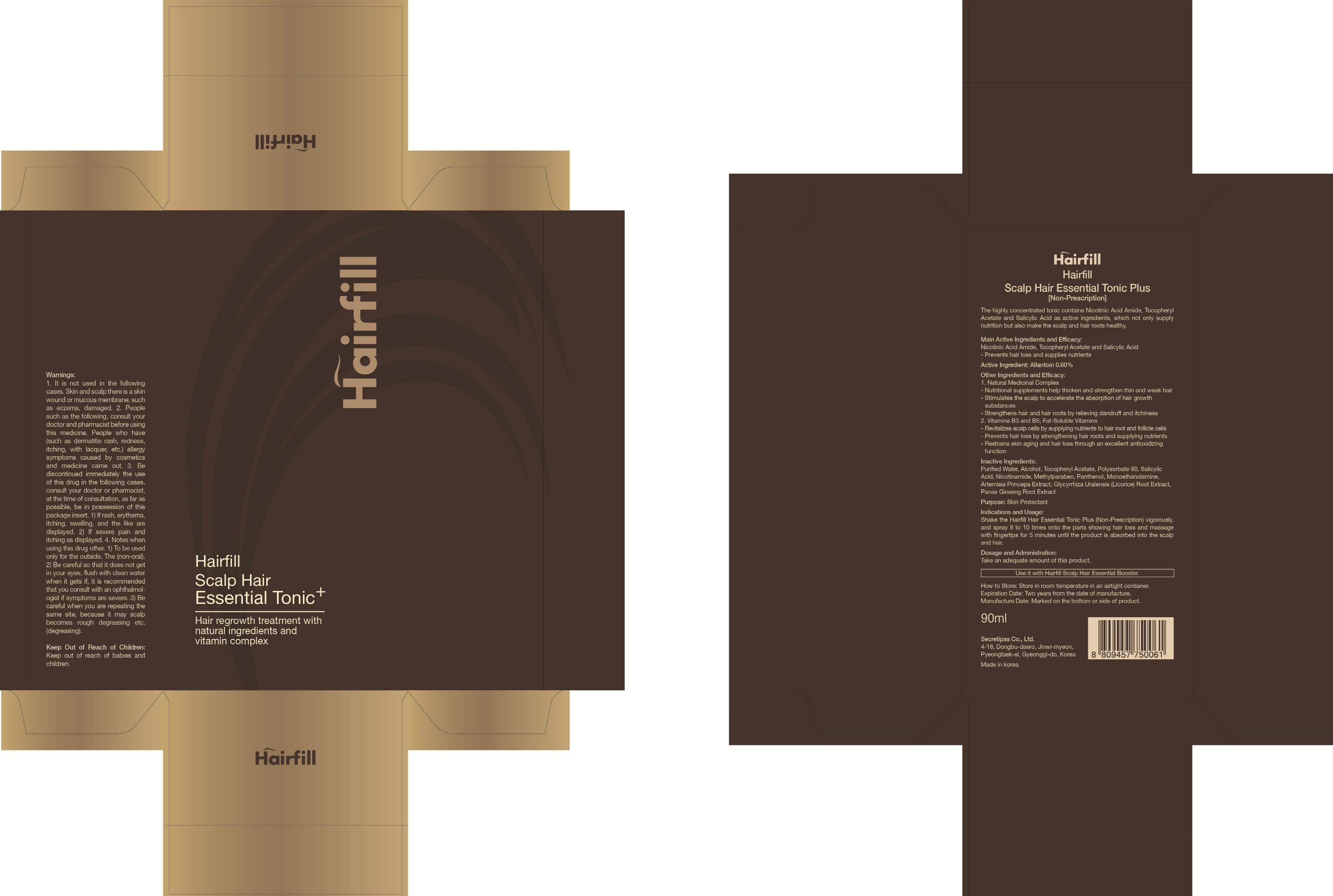 DRUG LABEL: HAIRFILL SCALP HAIR ESSENTIAL TONIC PLUS
NDC: 69684-300 | Form: LIQUID
Manufacturer: SECRETIPSS CO., LTD.
Category: otc | Type: HUMAN OTC DRUG LABEL
Date: 20150609

ACTIVE INGREDIENTS: Allantoin 0.54 mg/90 mL
INACTIVE INGREDIENTS: WATER; ALCOHOL

ACTIVE INGREDIENT

Active Ingredient: Allantoin 0.60%

INACTIVE INGREDIENT

Inactive Ingredients: Purified Water, Alcohol, Tocopheryl Acetate, Polysorbate 80, Salicylic Acid, Nicotinamide, Methylparaben, Panthenol, Monoethanolamine, Artemisia Princeps Extract, Glycyrrhiza Uralensis (Licorice) Root Extract, Panax Ginseng Root Extract

PURPOSE

Purpose: Skin Protectant

WARNINGS

Warnings: 1. It is not used in the following cases. Skin and scalp there is a skin wound or mucous membrane, such as eczema, damaged 2. People such as the following, consult your doctor and pharmacist before using this medicine People who have (such as dermatitis rash, redness, itching, with lacquer, etc.) allergy symptoms caused by cosmetics and medicine came out 3. Be discontinued immediately the use of this drug in the following cases, consult your doctor or pharmacist, at the time of consultation, as far as possible, be in possession of this package insert 1) If rash, erythema, itching, swelling, and the like are displayed 2) If severe pain and itching as displayed 4. Notes when using this drug other 1) To be used only for the outside. The (non-oral) 2) Be careful so that it does not get in your eyes, flush with clean water when it gets if, it is recommended that you consult with an ophthalmologist if symptoms are severe. 3) Be careful when you are repeating the same site, because it may scalp becomes rough degreasing etc. (degreasing).

KEEP OUT OF REACH OF CHILDREN

Keep out of reach of babies and children.

INDICATIONS & USAGE

Indications and Usage: Shake the Hairfill Scalp Hair Essential Tonic Plus vigorously, and spray 8 to 10 times onto the parts showing hair loss and massage with fingertips for 5 minutes until the product is absorbed into the scalp and hair.

DOSAGE & ADMINISTRATION

Dosage and Administration: Take an adequate amount of this product.